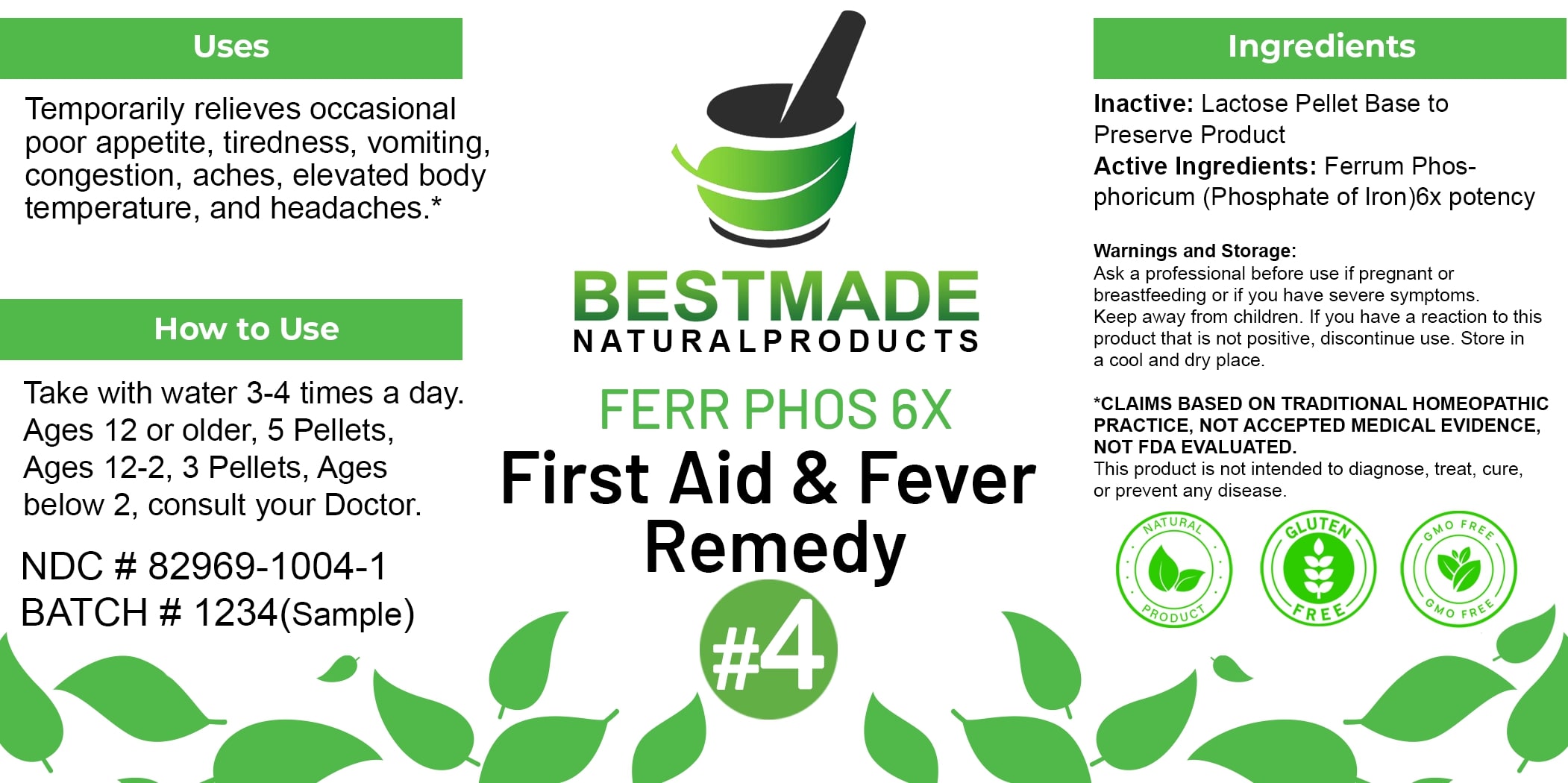 DRUG LABEL: Bestmade Natural Products Ferr Phos
NDC: 82969-1004 | Form: TABLET, SOLUBLE
Manufacturer: Bestmade Natural Products
Category: homeopathic | Type: HUMAN OTC DRUG LABEL
Date: 20250321

ACTIVE INGREDIENTS: FERRIC PYROPHOSPHATE 6 [hp_X]/6 [hp_X]
INACTIVE INGREDIENTS: LACTOSE 6 [hp_X]/6 [hp_X]

DOSAGE AND ADMINISTRATION

How to Use

Take with water 3-4 times a day. Ages 12 or older, 5 Pellets, Ages 12-2, 3 Pellets, Ages below 2, consult your Doctor.

INACTIVE INGREDIENT

Ingredients

Inactive: Lactose Pellet Base to Preserve Product

Uses

Temporarily relieves occasional poor appetite, tiredness, vomiting, congestion, aches, elevated body temperature, and headaches.*

*CLAIMS BASED ON TRADITIONAL HOMEOPATHIC PRACTICE, NOT ACCEPTED MEDICAL EVIDENCE. NOT FDA EVALUATED.

This product is not intended to diagnose, treat, cure, or prevent any disease.

KEEP OUT OF REACH OF CHILDREN

Warnings and Storage:

Ask a professional before use if pregnant or breastfeeding or if you have severe symptoms. Keep away from children. If you have a reaction to this product that is not positive, discontinue use. Store in a cool and dry place.

Uses

Temporarily relieves occasional poor appetite, tiredness, vomiting, congestion, aches, elevated body temperature, and headaches.*

*CLAIMS BASED ON TRADITIONAL HOMEOPATHIC PRACTICE, NOT ACCEPTED MEDICAL EVIDENCE. NOT FDA EVALUATED.

This product is not intended to diagnose, treat, cure, or prevent any disease.

ACTIVE INGREDIENT

Active Ingredients: Ferrum Phosphoricum (Phosphate of Iron) 6x potency

Warnings and Storage:

Ask a professional before use if pregnant or breastfeeding or if you have severe symptoms. Keep away from children. If you have a reaction to this product that is not positive, discontinue use. Store in a cool and dry place.

*CLAIMS BASED ON TRADITIONAL HOMEOPATHIC PRACTICE, NOT ACCEPTED MEDICAL EVIDENCE. NOT FDA EVALUATED.

This product is not intended to diagnose, treat, cure, or prevent any disease.

Entire package label